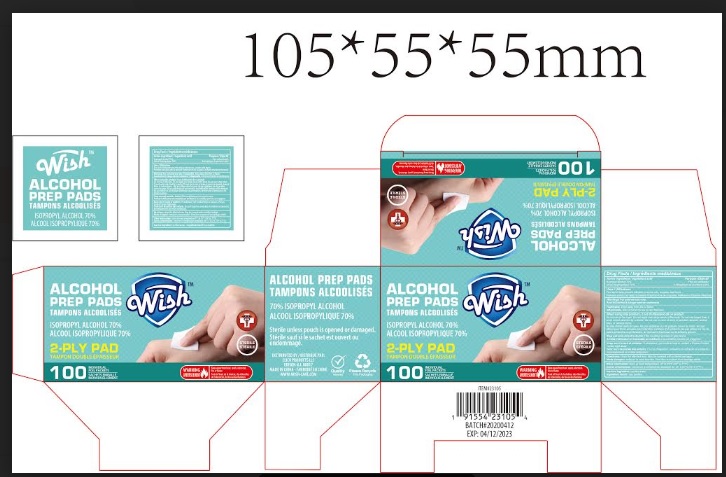 DRUG LABEL: Alcohol Prep Pad Sterile
NDC: 71611-020 | Form: SWAB
Manufacturer: CLICK PRODUCTS LLC
Category: otc | Type: HUMAN OTC DRUG LABEL
Date: 20200529

ACTIVE INGREDIENTS: ISOPROPYL ALCOHOL 0.7 mL/1 mL
INACTIVE INGREDIENTS: WATER

Wish Alcohol Prep Pad: Sterile

Active Ingredients

Isopropyl Alcohol 70%

Purpose

First aid Antiseptic

Use

First aid to help prevent infection in minor cuts,scrapes and burns.

Warnings

- For external use only
- Flammable, keep away from fire or flame

Do Not Use

- with electrocautery procedures
- In the eyes. If contact occurs, flush eyes with water
- Do not apply over large areas of the body.
- Do not use longer than 1 week unless directed by a doctor.
- Do not use in case of deep or puncture wounds,animal bites, or serious burns.

Stop Use

Stop use and consult a doctor if the condition persists or gets worse.

Keep out of reach of children.

If swallowed get medical help or contact a Poison Control Center right away.

Directions

- Clean the affected area.May be covered with a sterile banage.

Other Information

Store at room temperature 15° - 25°C (59° - 77° F)

Inactive Ingredient

purified water